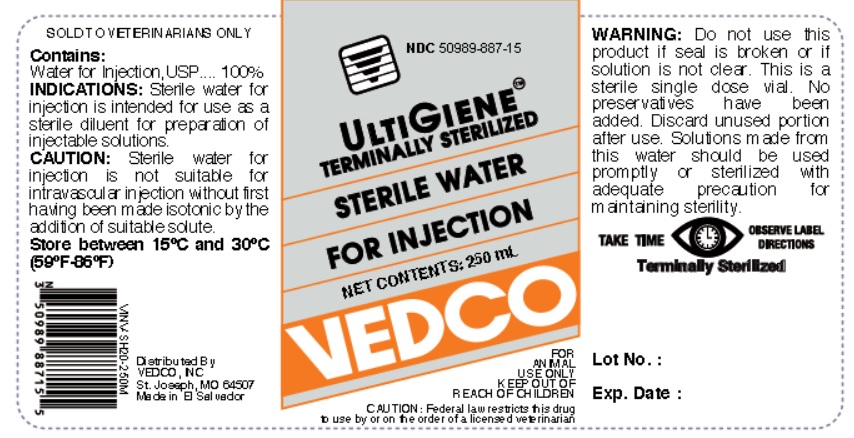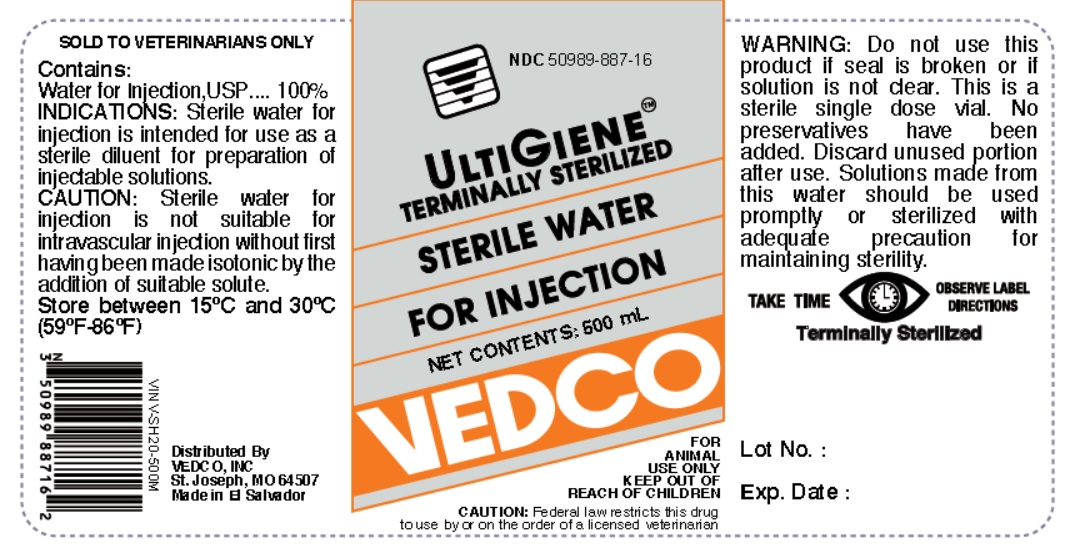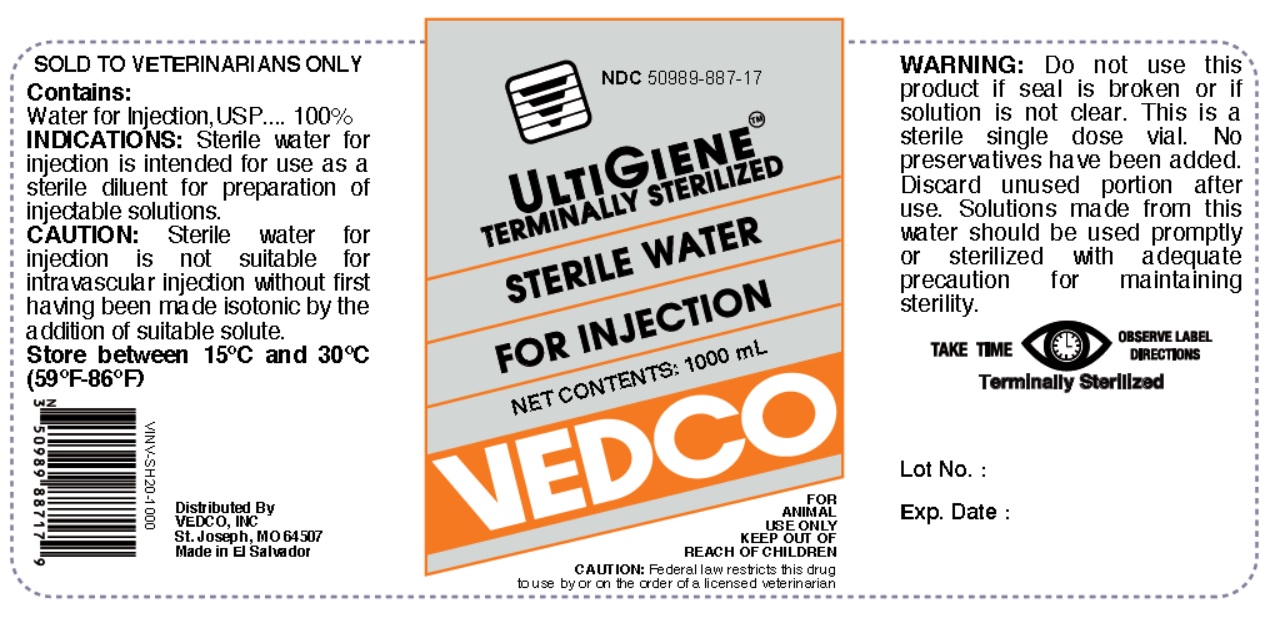 DRUG LABEL: Sterile Water
NDC: 50989-887 | Form: INJECTION
Manufacturer: Vedco
Category: animal | Type: PRESCRIPTION ANIMAL DRUG LABEL
Date: 20190312

ACTIVE INGREDIENTS: WATER 100 mL/100 mL

STERILE WATER FOR INJECTION

STERILE WATER- sterile water for injection injection

Vedco

Disclaimer: This drug has not been found by FDA to be safe and effective, and this labeling has not been approved by FDA.

STERILE WATER FOR INJECTION

FOR ANIMAL USE ONLY

SOLD TO VETERINARIANS ONLY

ACTIVE INGREDIENT

Contains:

Water For Injection, USP................ 100%

INDICATIONS:

Sterile water for injection is intended for use as a sterile diluent for preparation of injectable solutions.

CAUTION:

Sterile water for injection is not suitable for intravascular injection without first having been made isotonic by the addition of suitable solute.

STORAGE

Store between 15°C and 30°C (59°F-86°F).

KEEP OUT OF REACH OF CHILDREN

CAUTION:

Federal law restricts this drug to use by or on the order of a licensed veterinarian.

WARNING:

Do not use this product if seal is broken or if solution is not clear. This is a sterile single dose vial. No preservatives have been added. Discard unused portion after use. Solutions made from this water should be used promptly or sterilized with adequate precautions for maintaining sterility.

DOSAGE AND ADMINISTRATION

TAKE TIME OBSERVE LABEL DIRECTIONS

INFORMATION FOR OWNERS/CAREGIVERS

Distributed By

VEDCO, INC.

St. Joseph, MO 64507
Made in El Salvador

STERILE SOLUTION
CONTENT | NDC | VINV #
250 mL | 50989-887-15 | VINV-SH20-250M
500 mL | 50989-887-16 | VINV-SH20-500M
1000 mL | 50989-887-17 | VINV-SH20-1000

PRINCIPAL DISPLAY PANEL

NDC 50989-887-15

ULTIGIENE TERMINALLY STERILIZED

STERILE WATER FOR INJECTION

NET CONTENTS: 250 mL

VEDCO

FOR ANIMAL USE ONLY

KEEP OUT OF REACH OF CHILDREN

CAUTION: Federal law restricts this drug to use by or on the order of a licensed veterinarian

NDC 50989-887-16

ULTIGIENE TERMINALLY STERILIZED

STERILE WATER FOR INJECTION

NET CONTENTS: 500 mL

VEDCO

FOR ANIMAL USE ONLY

KEEP OUT OF REACH OF CHILDREN

CAUTION: Federal law restricts this drug to use by or on the order of a licensed veterinarian

NDC 50989-887-17

ULTIGIENE TERMINALLY STERILIZED

STERILE WATER FOR INJECTION

NET CONTENTS: 1000 mL

VEDCO

FOR ANIMAL USE ONLY

KEEP OUT OF REACH OF CHILDREN

CAUTION: Federal law restricts this drug to use by or on the order of a licensed veterinarian